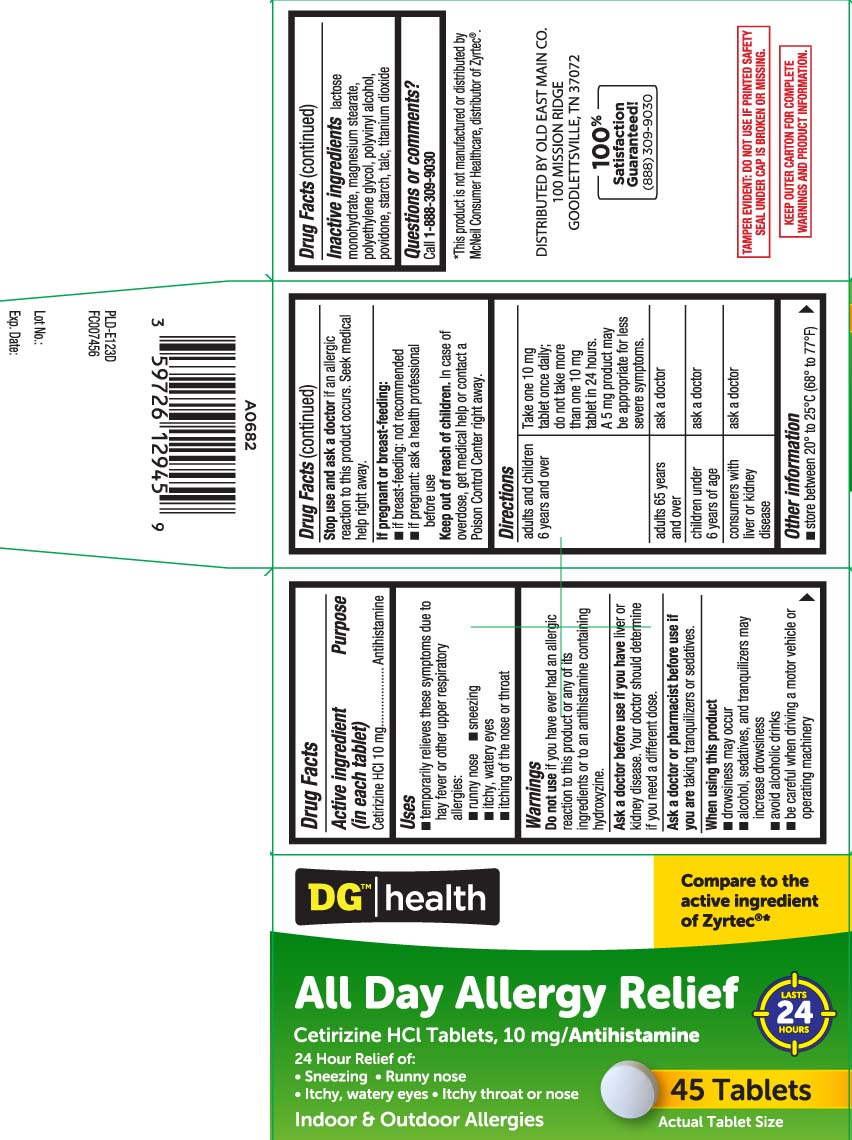 DRUG LABEL: Allergy Relief
NDC: 55910-129 | Form: TABLET
Manufacturer: Dolgencorp, Inc.  (DOLLAR GENERAL & REXALL)
Category: otc | Type: HUMAN OTC DRUG LABEL
Date: 20250701

ACTIVE INGREDIENTS: CETIRIZINE HYDROCHLORIDE 10 mg/1 1
INACTIVE INGREDIENTS: LACTOSE MONOHYDRATE; MAGNESIUM STEARATE; POLYETHYLENE GLYCOL, UNSPECIFIED; POVIDONE; STARCH, CORN; TALC; TITANIUM DIOXIDE; POLYVINYL ALCOHOL, UNSPECIFIED

Drug Facts

Active ingredient (in each tablet)

Cetirizine HCl 10 mg

Purpose

Antihistamine

Uses

- temporarily relieves these symptoms due to hay fever or other upper respiratory allergies:
  - runny nose
- sneezing
- itchy, watery eyes
- itching of the nose or throat

Warnings

Do not use

if you have ever had an allergic reaction to this product or any of its ingredients or to an antihistamine containing hydroxyzine.

Ask a doctor before use if you have

liver or kidney disease. Your doctor should determine if you need a different dose.

Ask a doctor or pharmacist before use if you are

taking tranquilizers or sedatives.

When using this product

- drowsiness may occur
- alcohol, sedatives, and tranquilizers may increase drowsiness
- avoid alcohol drinks
- be careful when driving a motor vehicle or operating machinery

Stop use and ask a doctor if

an allergic reaction to this product occurs. Seek medical help right away.

If pregnant or breast-feeding:

- if breast-feeding: not recommended
- if pregnant: ask a health professional before use

Keep out of reach of children.

In case of overdose, get medical help or contact a Poison Control Center right away.

Directions

adults and children 6 years and over | Take one 10 mg tablet once daily; do not take more than one 10 mg tablet in 24 hours. A 5 mg product may be appropriate for less severe symptoms.
adults 65 years and over | ask a doctor
children under 6 years of age | ask a doctor
consumers with liver or kidney disease | ask a doctor

Other information

- store between 20º to 25ºC (68º to 77ºF)

Inactive ingredients

lactose monohydrate, magnesium stearate, polyethylene glycol, polyvinyl alcohol, povidone, starch, talc, titanium dioxide

Questions or comments?

Call 1-888-309-9030

Principal Display Panel

Compare to the active ingredient of Zyrtec®*

All Day Allergy Relief

Cetirizine HCI Tablets,10 mg / Antihistamine

24-Hour Relief of:

- Sneezing
- Running nose
- Itchy, watery eyes
- Itchy nose or throat

Indoor & Outdoor Allergies

Tablets

*This product is not manufactured or distributed by McNeil Consumer Healthcare, distributor of Zyrtec®.

TAMPER EVIDENT: DO NOT USE IF PRINTED SAFETY SEAL UNDER CAP IS BROKEN OR MISSING.

KEEP OUTER CARTON FOR COMPLETE WARNINGS AND PRODUCT INFORMATION.

DISTRIBUTED BY OLD EAST MAIN CO.

100 MISSION RIDGE

GOODLETTSVILLE, TN 37072

Product Label

DOLLAR GENERAL All Day Allergy Relief